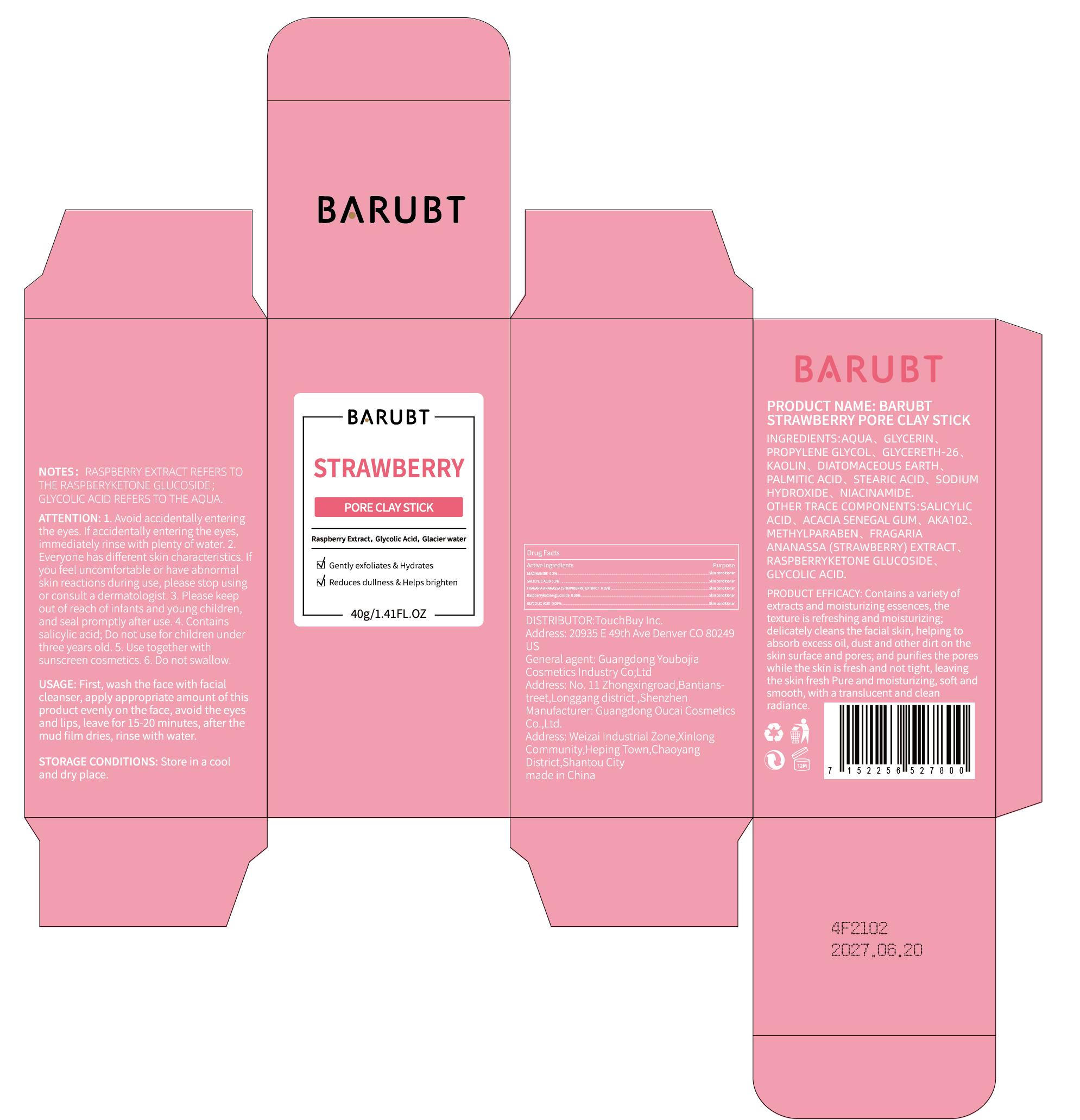 DRUG LABEL: BARUBT Strawberry Pore Clay Stick
NDC: 84712-018 | Form: PASTE
Manufacturer: Guangdong Youbaijia Cosmetic Industry Co., Ltd
Category: otc | Type: HUMAN OTC DRUG LABEL
Date: 20240917

ACTIVE INGREDIENTS: GLYCOLIC ACID 0.02 g/40 g; SALICYLIC ACID 0.04 g/40 g; STRAWBERRY 0.02 g/40 g; RASPBERRYKETONE GLUCOSIDE 0.02 g/40 g; NIACINAMIDE 0.08 g/40 g
INACTIVE INGREDIENTS: KAOLIN 3.2 g/40 g; GLYCERETH-26 3.2 g/40 g

ACTIVE INGREDIENT

SALICYLIC ACID 0.1%
NIACINAMIDE 0.2%
FRAGARIA ANANASSA (STRAWBERRY) EXTRACT 0.05%
Raspberryketone glucoside 0.05%
GLYCOLIC ACID 0.05%

INACTIVE INGREDIENT

AQUA
GLYCERIN
PROPYLENE GLYCOL
GLYCERETH-26
KAOLIN
DIATOMACEOUS EARTH
PALMITIC ACID
STEARIC ACID
SODIUM HYDROXIDE
ACACIA SENEGAL GUM
AKA102
METHYLPARABEN

Do not use on damaged skin.

Keep away from children. Do not swallow.

PURPOSE

moisturizing, cleaning

QUESTIONS

Contact name: Jessie Peng
Company phone number: +1 818 579 7288
Company e-mail: jessie@registeragentllc.com

STOP USE

lf you feel uncomfortable or have abnommal skin reactions during use, please stop using or consult a dermatologist.

WHEN USING

Avoid accidentally entering the eyes. lf accidentally entering the eyes, immediately rinse with plenty of water.

STORAGE AND HANDLING

Store in a cool and dry place.

INDICATIONS AND USAGE

Contains a variety of extracts and moisturizing essences, the texture is refreshing and moisturizing; delicately cleans the facial skin, helping to absorb excess oil, dust and other dirt on the skin surface and pores; and purifies the pores while the skin is fresh and not tight, leaving the skin fresh Pure and moisturizing, soft and smooth,with a translucent and clean radiance

DOSAGE AND ADMINISTRATION

First, wash the face with facial cleanser, apply appropriate amount of this product evenly on the face, avoid the eyes and lips, leave for 15-20 minutes, after the mud film dries, rinse with water

WARNINGS

For external use only.